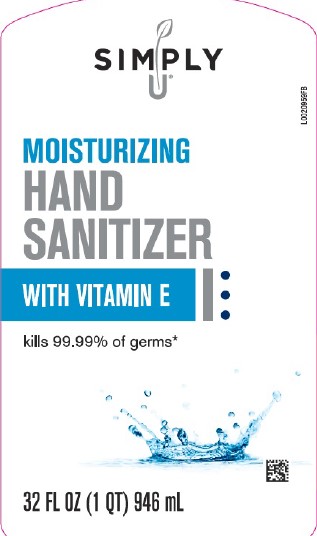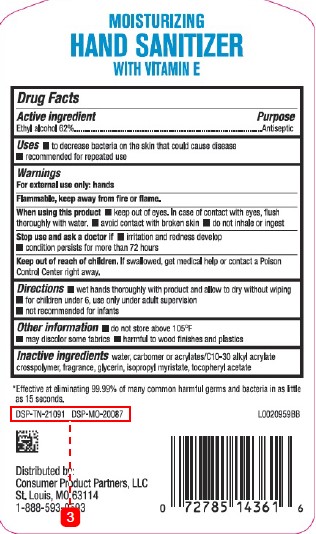 DRUG LABEL: Alcohol
NDC: 11344-849 | Form: LIQUID
Manufacturer: Consumer Product Partners, LLC
Category: otc | Type: HUMAN OTC DRUG LABEL
Date: 20250227

ACTIVE INGREDIENTS: ALCOHOL 62 mL/100 mL
INACTIVE INGREDIENTS: WATER; CARBOMER HOMOPOLYMER, UNSPECIFIED TYPE; CARBOMER INTERPOLYMER TYPE A (ALLYL SUCROSE CROSSLINKED); GLYCERIN; ISOPROPYL MYRISTATE; TOCOPHEROL

Simply U 849.001/849AB-AG,BA
Moisturizing Hand Sanitizer

Claims

MOISTURIZING HAND SANITIZER WITH VITAMIN E

Active ingredient

Ethyl alcohol 62%

Purpose

Antiseptic

Uses

- to decrease bacteria on the skin that could cause disease
- recommended for repeated use

Warnings

For exterenal use only: hands

Flammable, keep away from fire or flame.

When using this product

- keep out of eyes. In case of contact with eyes, flush thoroughly with water.
- avoid contact with broken skin
- do not inhale or ingest

Stop use and ask a doctor if

- irritation and redness develop
- condition persists for more than 72 hours

Keep out of reach of children.

If swallowed, get medical help or contact a Poison Control Center right away.

Directions

- wet hands thoroughly with product and allow to dry without wiping
- for children under 6, use only under adult supervision
- not recommended for infants

Other information

- do not store above 105⁰F
- may discolor some fabrics
- harmful to wood finishes and plastics

Inactive ingredients

water, carbomer or acrylates/C10-30 alkyl acrylate crosspolymer, fragrance, glycerin, isopropyl myristate, tocopheryl acetate

Claims

*Effective at eliminating 99.99% of many common harmful germs and bacteria in as little as 15 seconds.

ADVERSE REACTION

DSP-TN-21091 DSP-MO-20087

Distributed By:

Consumer Product Partners, LLC

St. Louis, MO 63114

1-888-593-0593

Principal panel display

SIMPLY

U ®

Moisturizing

Hand

Sanitizer

With Vitamin E

Kills 99.99% of germs*

32 FL OZ (1 QT) 946 mL